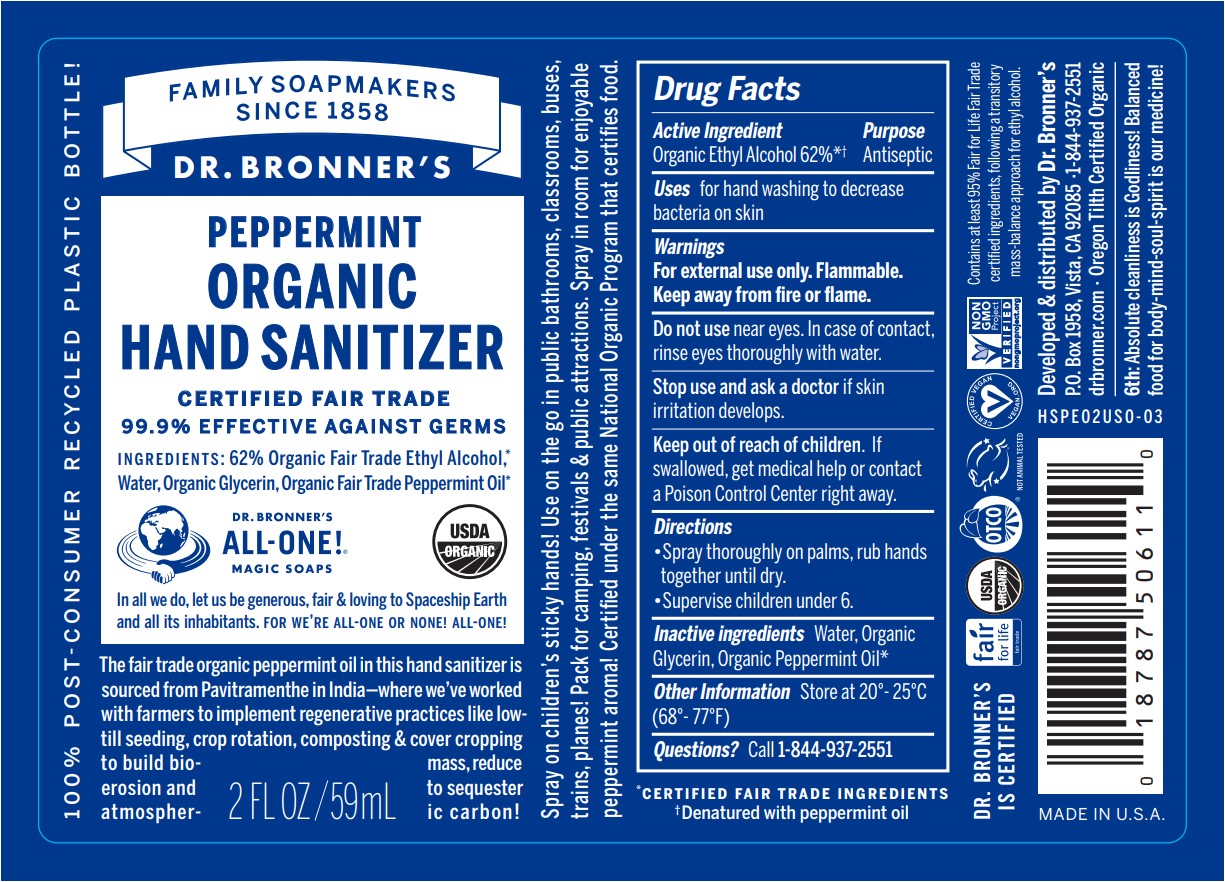 DRUG LABEL: Dr Bronners
NDC: 73333-160 | Form: LIQUID
Manufacturer: Nutrix International, LLC.
Category: otc | Type: HUMAN OTC DRUG LABEL
Date: 20220510

ACTIVE INGREDIENTS: ALCOHOL 0.7 g/59 g
INACTIVE INGREDIENTS: PEPPERMINT OIL 0.002 g/59 g; GLYCERIN 0.01 g/59 g; WATER 0.288 g/59 g

Dr Bronner's Hand Sanitizer Peppermint

Active Ingredient

ETHYL ALCOHOL (ORGANIC) 62%

PURPOSE:

ANTISEPTIC

USES:

FOR HAND WASHING TO DECREASE BACTERIA ON SKIN.

WARNINGS:

FOR EXTERNAL USE ONLY. FLAMMABLE, KEEP AWAY FROM FIRE OR FLAME.

DO NOT USE NEAR EYES. IN CASE OF CONTACT, RINSE EYES THOROUGHLY WITH WATER.

INACTIVE INGREDIENTS

WATER, ORGANIC GLYCERIN, ORGANIC PEPPERMINT OIL

KEEP OUT OF REACH OF CHILDREN. IF SWALLOWED, GET MEDICAL HELP OR CONTACT A POISON CONTROL CENTER RIGHT AWAY.

DO NOT USE NEAR EYES. IN CASE OF CONTACT, RINSE EYES THOROUGHLY WITH WATER.

STOP USE

STOP USE AND ASK A DOCTOR IF SKIN IRRITATION DEVELOPS.

DIRECTIONS

SPRAY ON PALM, RUB HANDS TOGETHER. SUPERVISE CHILDREN UNDER 6.

OTHER INFORMATION

STORE AT 20° - 25°C (68° - 77°F)

QUESTIONS?

CALL 760-743-2211

DISPLAY PANEL

LABEL